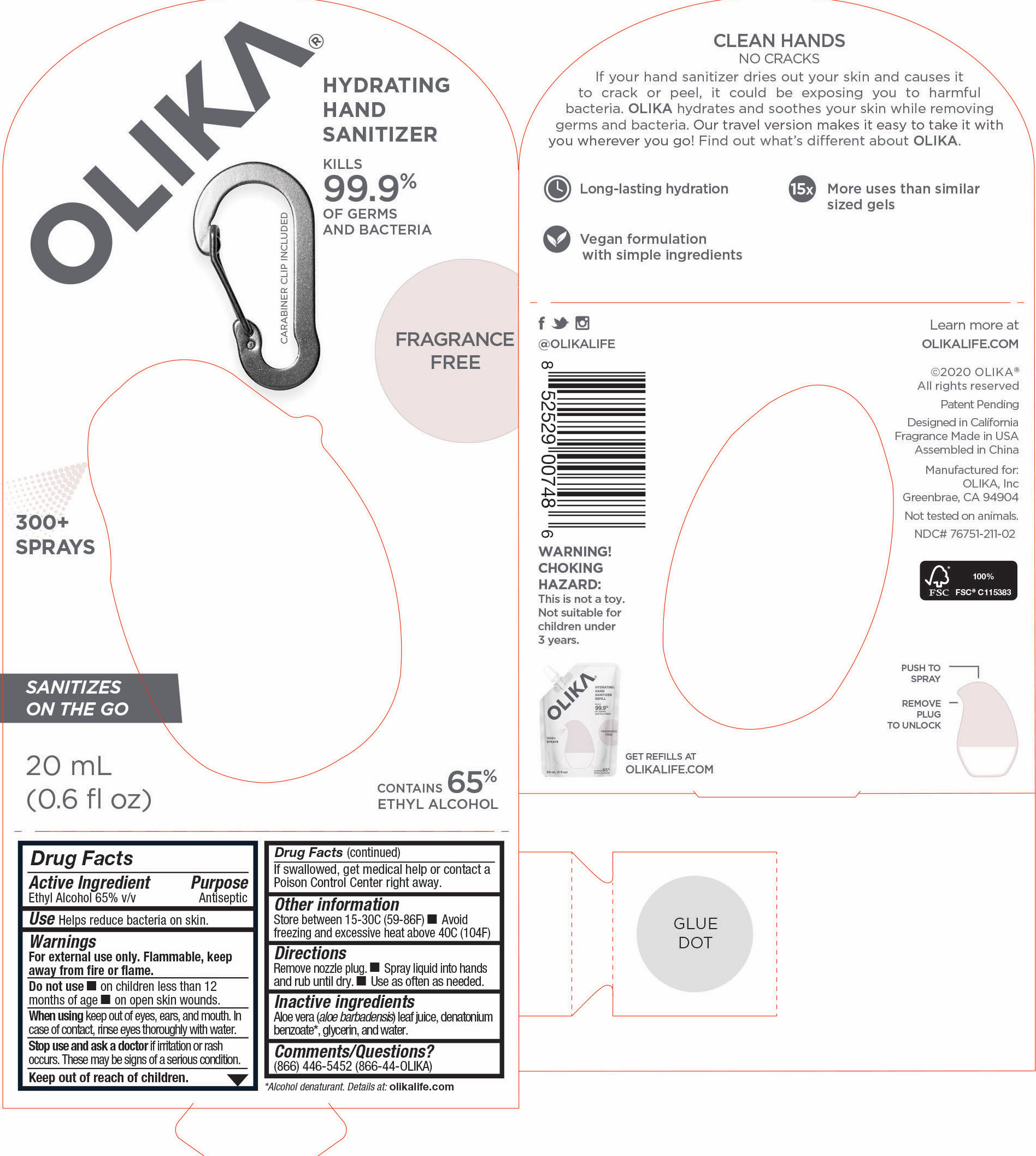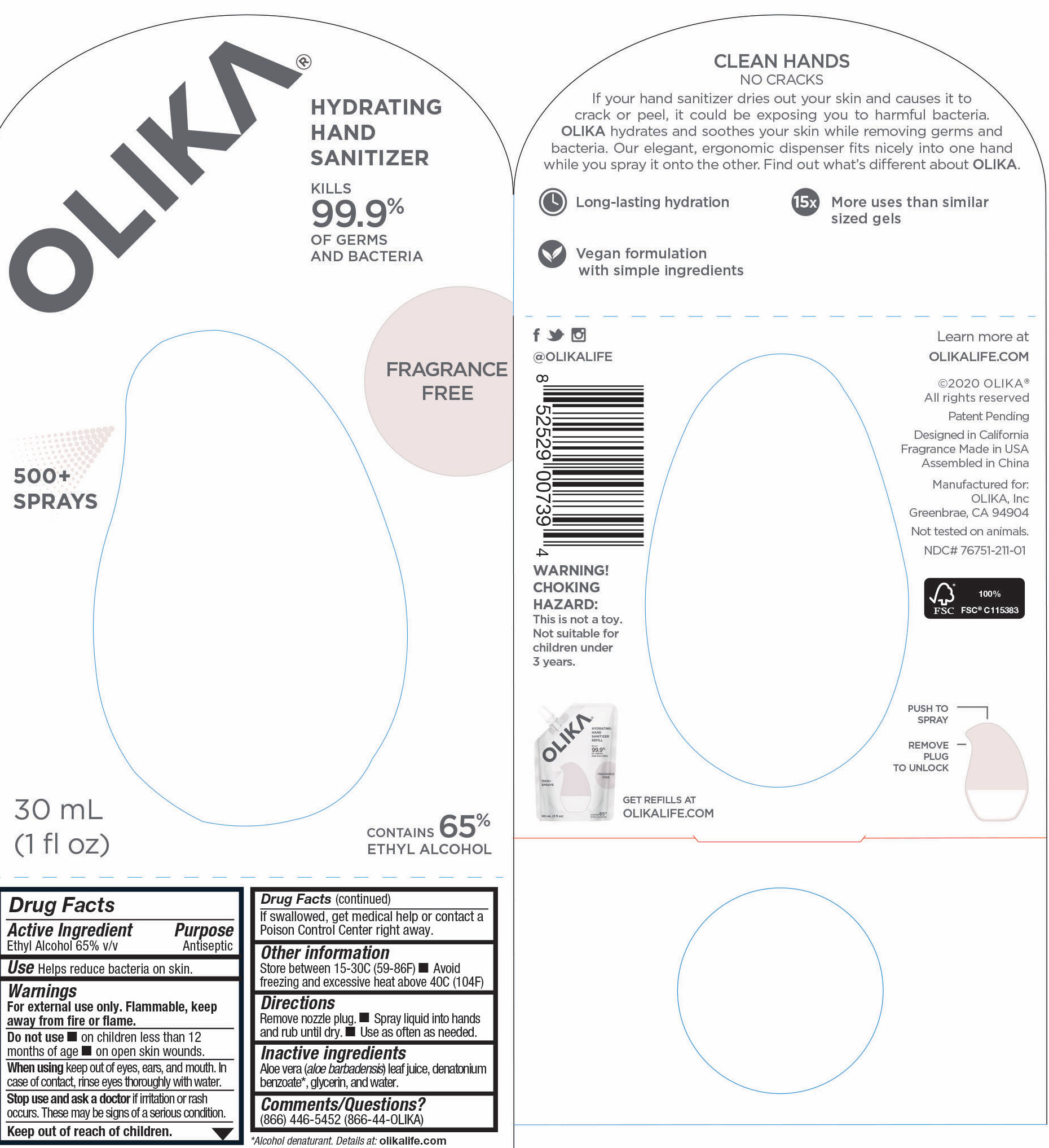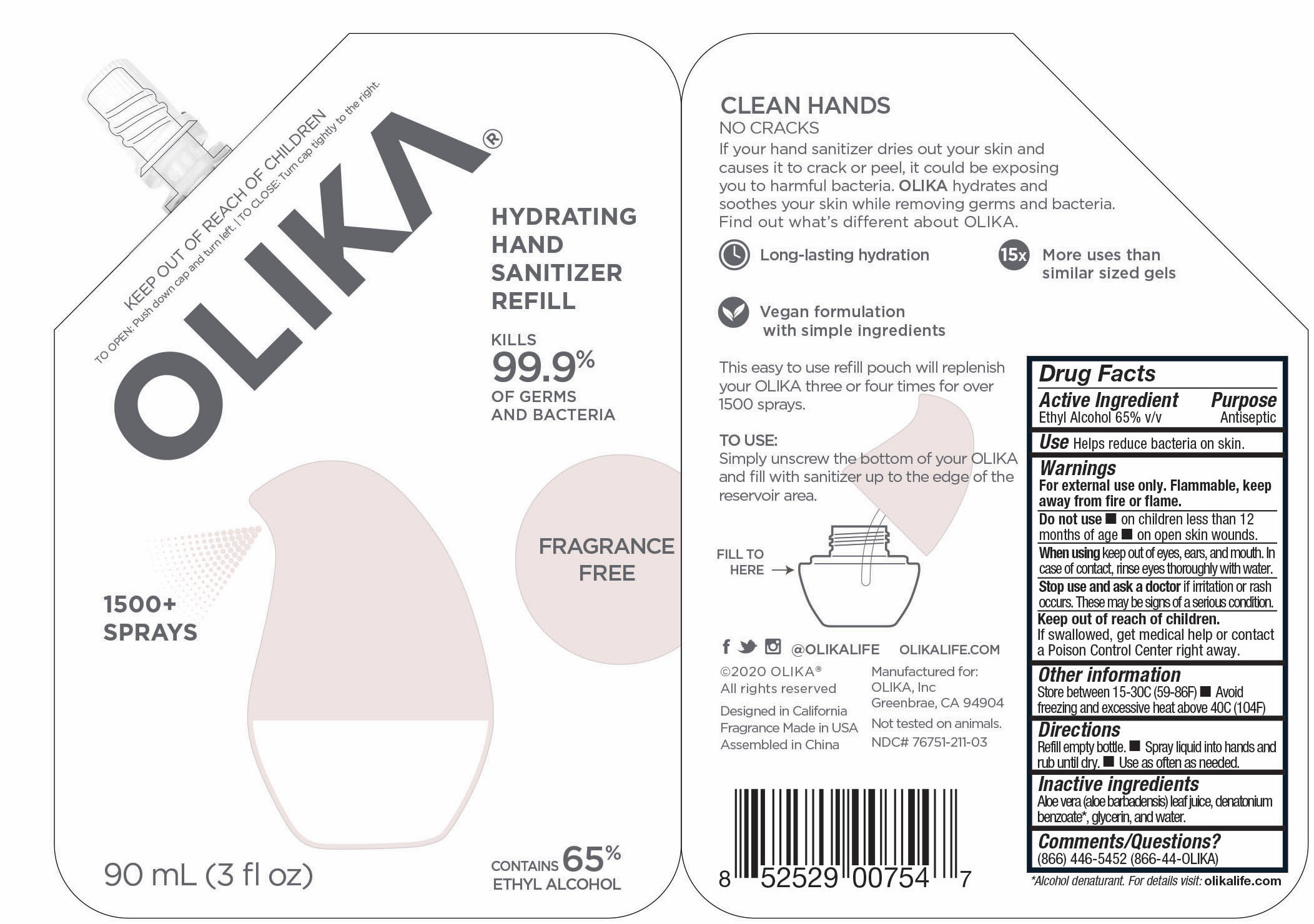 DRUG LABEL: Olika Hand Sanitizer Fragrance Free
NDC: 76751-211 | Form: LIQUID
Manufacturer: Perkin and Perkin LLC
Category: otc | Type: HUMAN OTC DRUG LABEL
Date: 20211220

ACTIVE INGREDIENTS: ALCOHOL 65 mL/100 mL
INACTIVE INGREDIENTS: GLYCERIN 4.2 mL/100 mL; ALOE VERA LEAF 0.25 mL/100 mL; WATER 30.55 mL/100 mL

OLIKA Hand Sanitizer Fragrane Free

This is a hand sanitizer manufactured according to the 1994 tentative final monograph for hand sanitizers and antiseptics.

The hand sanitizer is manufactured using only the following United States Pharmacopoeia (USP) or Food Chemical Codex (FCC) grade ingredients in the preparation of the product. Final formulation finished product testing was performed to confirm efficacy.

1. Alcohol (ethanol) (USP) (65%, volume/volume (v/v)) in an aqueous solution denatured according to Alcohol and Tobacco Tax and Trade Bureau regulations in 27 CFR part 20.

The formulation comes in 3 package sizes 20 mL, 30 mL, and 90 mL.

Active Ingredient(s)

65% Ethyl Alcohol v/v Purpose: Antiseptic

Purpose

Antiseptic, Hand Sanitizer

Warnings

For external use only. Flammable. Keep away from heat or flame

Do not use

- in children less than 2 months of age
- on open skin wounds

When using this product keep out of eyes, ears, and mouth. In case of contact with eyes, rinse eyes thoroughly with water.
Stop use and ask a doctor if irritation or rash occurs. These may be signs of a serious condition.
Keep out of reach of children. If swallowed, get medical help or contact a Poison Control Center right away.

Stop use and ask a doctor if irritation or rash occurs. These may be signs of a serious condition.

Keep out of reach of children. If swallowed, get medical help or contact a Poison Control Center right away.

Other information

- Store between 15-30C (59-86F)
- Avoid freezing and excessive heat above 40C (104F)

Inactive ingredients

aloe barbadensis leaf extract, glycerin, purified water USP

denatonium benzoate as alcohol denaturant

Use

Hand Sanitizer to help reduce bacteria on skin.

Directions

Remove nozzle bead. Spray liquid into hands and rub until dry. Use as often as needed.

Information Panel

Learn more at Olikalife.com

(c)2020 Olika All Rights Reserved

Designed in California

Fragrance Made in USA

Assembled in China

Manufactured for Olika, Inc.

Greenbrae, CA 94904

NDC Code 76751-211-01

76751-211-01 Package Label - Principal Display Panel

30 mL 76751-211-01

76751-211-02 Package Label _Principal Display Panel

20 mL 76751-211-02

76751-211-03 Package Label_ Principal Display Panel

90 mL 76761-211-03